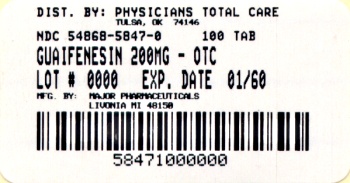 DRUG LABEL: Guaifenesin
NDC: 54868-5847 | Form: TABLET
Manufacturer: Physicians Total Care, Inc.
Category: otc | Type: HUMAN OTC DRUG LABEL
Date: 20120301

ACTIVE INGREDIENTS: GUAIFENESIN 200 mg/1 1
INACTIVE INGREDIENTS: MAGNESIUM STEARATE; MALTODEXTRIN; CELLULOSE, MICROCRYSTALLINE; POVIDONE; STEARIC ACID

Active ingredient (in each immediate-release tablet)

Guaifenesin 200 mg

Purpose

Expectorant

Use(s)

helps loosen phlegm (mucus) and thin bronchial secretions to rid the bronchial passageways of bothersome mucus and make coughs more productive

Warnings

Ask a doctor before use if you have

- persistent or chronic cough such as occurs with smoking, asthma, chronic bronchitis, or emphysema
- cough accompanied by too much phlegm (mucus)

Stop use and ask a doctor if

- cough lasts more than 7 days, comes back, or occurs with fever, rash, or persistent headache. These could be signs of a serious illness.

If pregnant or breast-feeding,

ask a health professional before use.

Keep out of reach of children.

In case of overdose, get medical help or contact a Poison Control Center right away.

Directions

- do not exceed 6 doses in 24 hours
- take with a full glass of water

adults and children 12 years of age and over | 1 to 2 tablets every 4 hours
children 6 to under 12 years of age | ½ to 1 tablet every; 4 hours
children under 6 years of age | consult a physician

Other information

- store at controlled room temperature 15º-30ºC (59º-86ºF)
- use by expiration date on package

Inactive ingredients

FD&C red #40 aluminum lake, magnesium stearate, maltodextrin, microcrystalline cellulose, povidone, silica gel, sodium starch glycolate, stearic acid

Questions?

To Report Adverse Drug Event Call: (800) 616-2471

Principal Display Panel

The product packaging shown below represents a sample of that currently in use. Additional packaging may also be available.
NDC 54868-5847-0
GUAIFENESIN TABLETS
Guaifenesin 200 mg
Expectorant

- Relieves Chest Congestion
- Thins and Loosens Mucus

100 Tablets Immediate Release
50844 REV0510A58812
Distributed by MAJOR PHARMACEUTICALS
31788 Enterprise Drive,
Livonia, MI 48150 USA
Re-Order No. 238163 M-17 Rev. 11/10
TAMPER EVIDENT: DO NOT USE IF IMPRINTED SAFETY SEAL UNDER CAP IS BROKEN OR MISSING
Additional barcode labeling by:
Physicians Total Care, Inc.
Tulsa, Oklahoma 74146